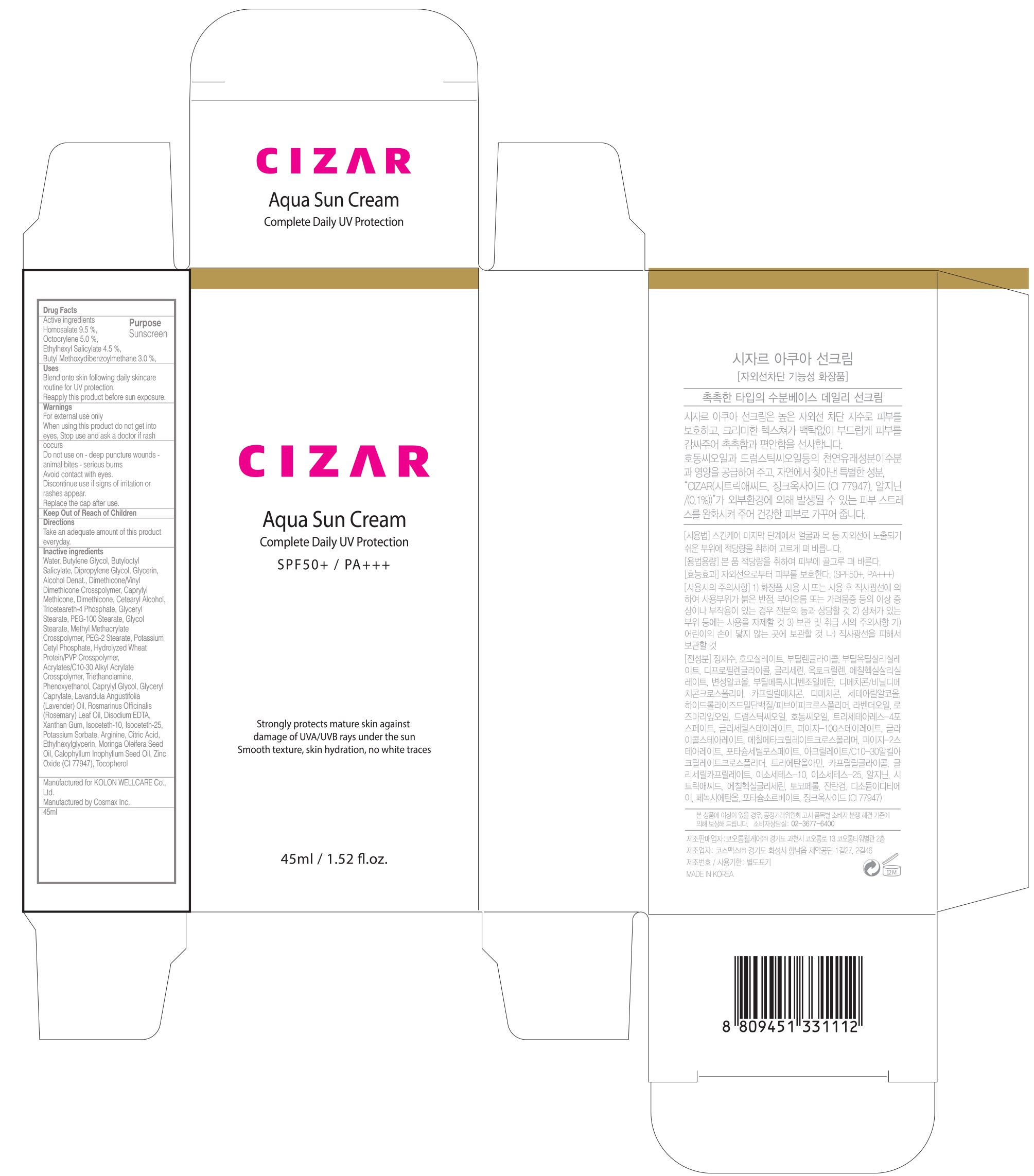 DRUG LABEL: CIZAR Aqua Sun
NDC: 71128-010 | Form: CREAM
Manufacturer: Tissuegene,inc
Category: otc | Type: HUMAN OTC DRUG LABEL
Date: 20181217

ACTIVE INGREDIENTS: Homosalate 4.27 g/45 mL; Octocrylene 2.25 g/45 mL; Octisalate 2.02 g/45 mL; Avobenzone 1.35 g/45 mL
INACTIVE INGREDIENTS: Water; Butylene Glycol

ACTIVE INGREDIENT

Active ingredients: Homosalate 9.5 %, Octocrylene 5.0 %, Ethylhexyl Salicylate 4.5 %, Butyl Methoxydibenzoylmethane 3.0 %

INACTIVE INGREDIENT

Inactive ingredients: Water, Butylene Glycol, Butyloctyl Salicylate, Dipropylene Glycol, Glycerin, Alcohol Denat., Dimethicone/Vinyl Dimethicone Crosspolymer, Caprylyl Methicone, Dimethicone, Cetearyl Alcohol, Triceteareth-4 Phosphate, Glyceryl Stearate, PEG-100 Stearate, Glycol Stearate, Methyl Methacrylate Crosspolymer, PEG-2 Stearate, Potassium Cetyl Phosphate, Hydrolyzed Wheat Protein/PVP Crosspolymer, Acrylates/C10-30 Alkyl Acrylate Crosspolymer, Triethanolamine, Phenoxyethanol, Caprylyl Glycol, Glyceryl Caprylate, Lavandula Angustifolia (Lavender) Oil, Rosmarinus Officinalis (Rosemary) Leaf Oil, Disodium EDTA, Xanthan Gum, Isoceteth-10, Isoceteth-25, Potassium Sorbate, Arginine, Citric Acid, Ethylhexylglycerin, Moringa Oleifera Seed Oil, Calophyllum Inophyllum Seed Oil, Zinc Oxide (CI 77947), Tocopherol

PURPOSE

Purpose: Sunscreen

WARNINGS

Warnings: For external use only When using this product do not get into eyes, Stop use and ask a doctor if rash occurs Do not use on - deep puncture wounds - animal bites - serious burns Avoid contact with eyes. Discontinue use if signs of irritation or rashes appear. Replace the cap after use. Keep Out of Reach of Children

DESCRIPTION

Uses: Blend onto skin following daily skincare routine for UV protection. Reapply this product before sun exposure.

Directions: Take an adequate amount of this product everyday.